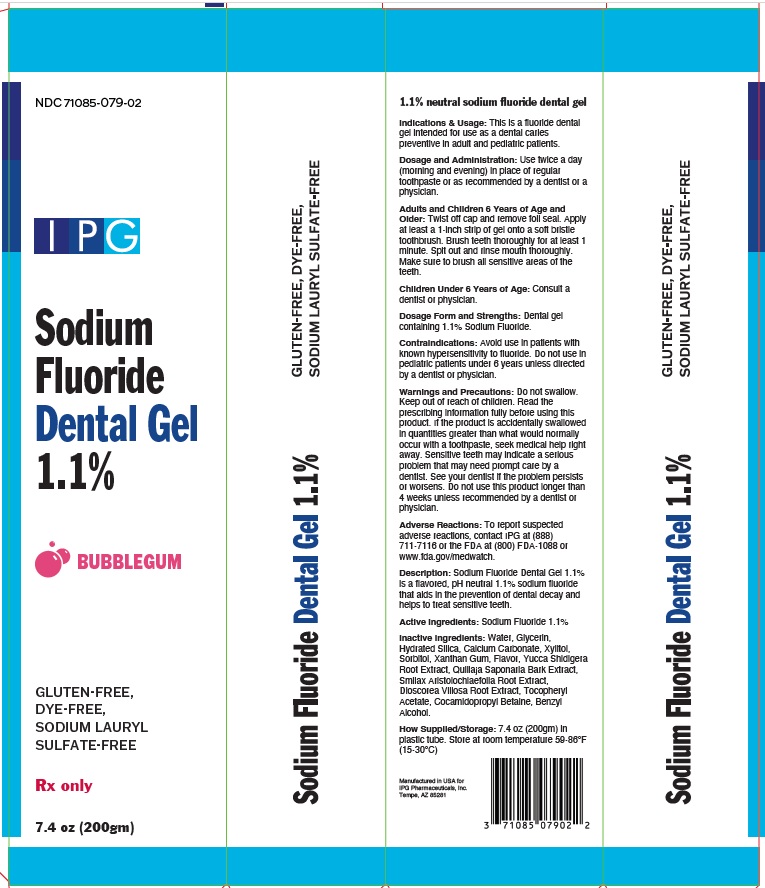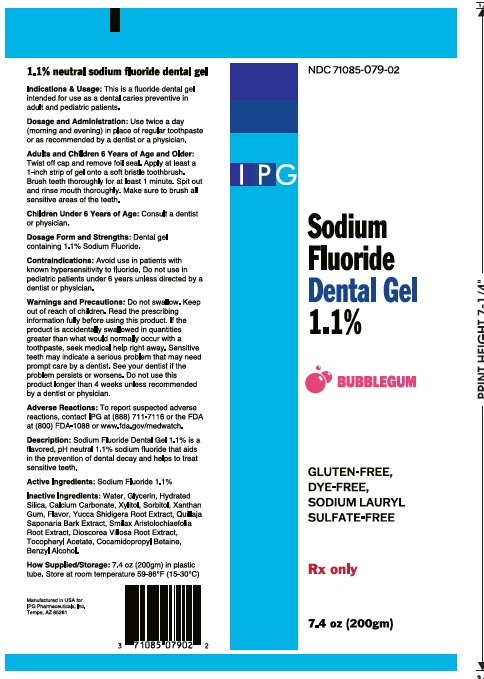 DRUG LABEL: Sodium Fluoride 1.1% Dental Gel BUBBLEGUM
NDC: 71085-079 | Form: GEL
Manufacturer: IPG PHARMACEUTICALS, INC.
Category: prescription | Type: HUMAN PRESCRIPTION DRUG LABEL
Date: 20250709

ACTIVE INGREDIENTS: SODIUM FLUORIDE 1.1 g/100 g
INACTIVE INGREDIENTS: WATER; GLYCERIN; HYDRATED SILICA; CALCIUM CARBONATE; XYLITOL; SORBITOL; XANTHAN GUM; YUCCA SCHIDIGERA WHOLE; QUILLAJA SAPONARIA BARK; SMILAX ARISTOLOCHIIFOLIA ROOT; DIOSCOREA VILLOSA ROOT; .ALPHA.-TOCOPHEROL ACETATE; COCAMIDOPROPYL BETAINE; BENZYL ALCOHOL

Active Ingredient

1.1% neutral sodium fluoride

PURPOSE

Sodium Fluoride Dental Gel 1.1% is a flavored, pH neutral 1.1% sodium fluoride that aids in the prevention of dental decay and helps to treat sensitive teeth.

Uses

This is a fluoride dental gel intended for use as a dental caries preventive in adults and pediatric patients.

Directions

Use twice a day (morning and evening) in place of regular toothpaste or as recommended by a dentist or a physician.

Adults and Children 6 Years of Age and Older: Twist off cap and remove foil seal. Apply at least a1-inch strip of gel onto a soft bristle toothbrush. Brush teeth thoroughly for at least 1 minute. Spit out and rinse mouth thoroughly. Make sure to brush all
sensitive areas of the teeth.

Dosage form and Strengths: Dental gel containing 1.1% sodium fluoride.

Warning

Contraindications: Avoid use in patients with known hypersensitivity to fluoride. Do not use in pediatric patients under 6 unless directed by a dentist or physician.
Warnings and Precautions: Do no swallow. Keep out of reach of children. Read the prescribing information fully before using this product. If the product is accidentally swallowed in quantities greater than would normally occur with a toothpaste, seek medical help right away. See your dentist if the problem persists or worsens. Do not use this product longer than 4 weeks unless recommended by a dentist or physician.
Adverse reactions: To report suspected

Adverse reactions, To report suspected adverse reactions, contact IPG Pharmaceuticals at (888) 711-7116 or the FDA at (800) FDA-1088 or www.fda.gov/medwatch.

Inactive ingredient

Water, Glycerin, Hydrated Silica, Calcium Carbonate, Xylitol, Sorbitol, Xanthan Gum, Flavor, Yucca Shidigera Root Extract, Quillaja
Saponaria Bark Extract, Smilax Aristolochiaefolia Root Extract, Dioscorea Villosa Root Extract, Tocopheryl Acetate, Cocamidopropyl Betaine,
Benzyl Alcohol.

How Supplied/Storage: 7.4 oz (200gm) in plastic tube. Store at room temperature 59-86°F (15-30°C)